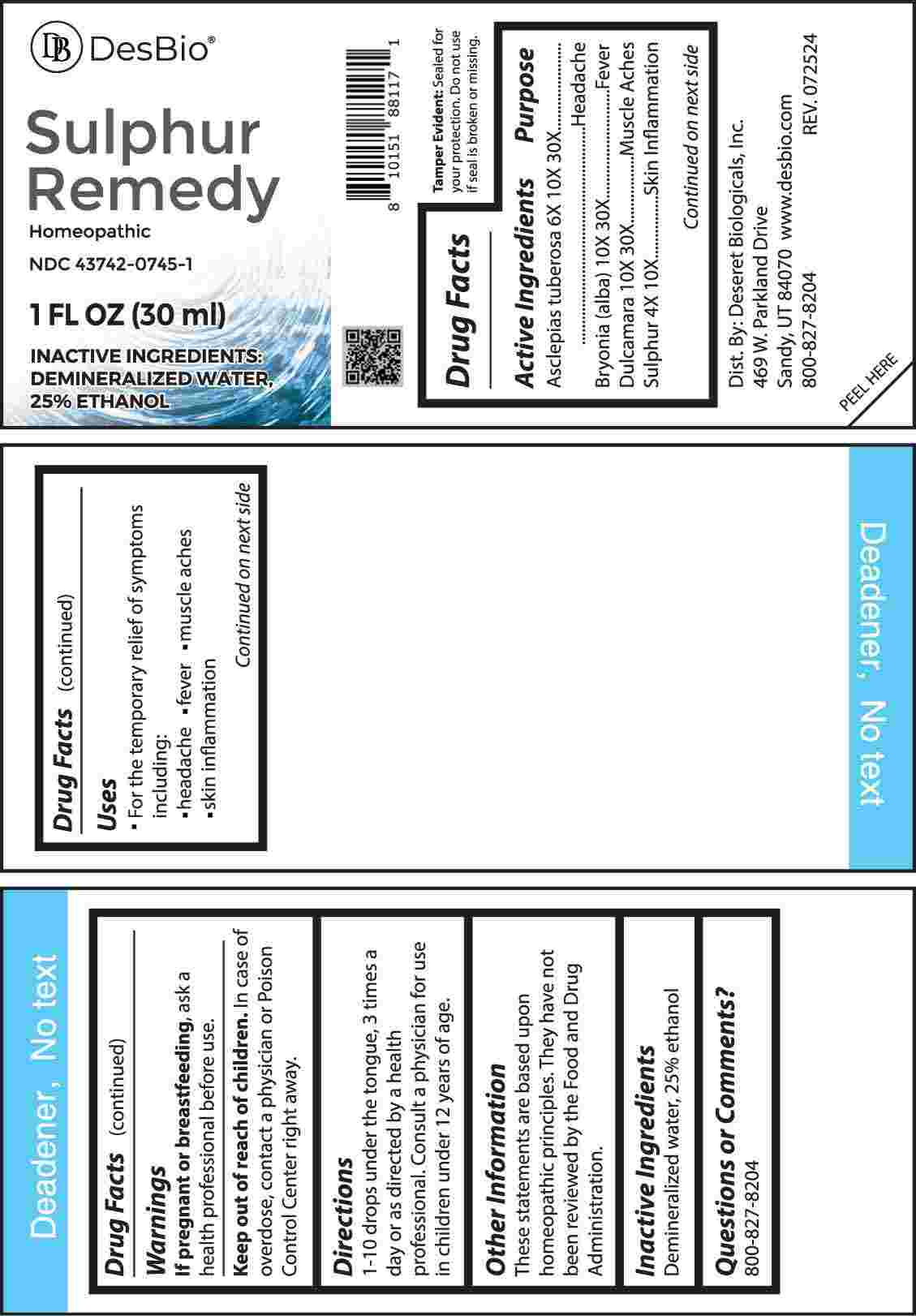 DRUG LABEL: Sulphur Remedy
NDC: 43742-0745 | Form: LIQUID
Manufacturer: Deseret Biologicals, Inc.
Category: homeopathic | Type: HUMAN OTC DRUG LABEL
Date: 20241023

ACTIVE INGREDIENTS: SULFUR 4 [hp_X]/1 mL; ASCLEPIAS TUBEROSA ROOT 6 [hp_X]/1 mL; BRYONIA ALBA ROOT 10 [hp_X]/1 mL; SOLANUM DULCAMARA STEM 10 [hp_X]/1 mL
INACTIVE INGREDIENTS: WATER; ALCOHOL

Drug Facts:

ACTIVE INGREDIENTS:

Asclepias Tuberosa 6X, 10X, 30X, Bryonia (Alba) 10X, 30X, Dulcamara 10X, 30X, Sulphur 4X, 10X.

PURPOSE:

Asclepias Tuberosa - Headache, Bryonia (Alba) - Fever, Dulcamara - Muscle Aches, Sulphur - Skin Inflammation

USES:

• For the temporary relief of symptoms including:

• headache • fever • muscle aches • skin inflammation

These statements are based upon homeopathic principles. They have not been reviewed by the Food and Drug Administration.

WARNINGS:

If pregnant or breast-feeding, ask a health professional before use.

Keep out of reach of children. In case of overdose, contact a physician or Poison Control Center right away.

Tamper Evident: Sealed for your protection. Do not use if seal is broken or missing.

KEEP OUT OF REACH OF CHILDREN:

In case of overdose, contact a physician or Poison Control Center right away.

DIRECTIONS:

1-10 drops under the tongue, 3 times a day or as directed by a health professional. Consult a physician for use in children under 12 years of age.

INACTIVE INGREDIENTS:

Demineralized water, 25% ethanol

QUESTIONS:

Dist. By: Deseret Biologicals, Inc.

469 W. Parkland Drive

Sandy, UT 84070

www.desbio.com

800-827-8204

PACKAGE LABEL DISPLAY:

DesBio

Sulphur Remedy

Homeopathic

NDC 43742-0745-1

1 FL OZ (30 ml)